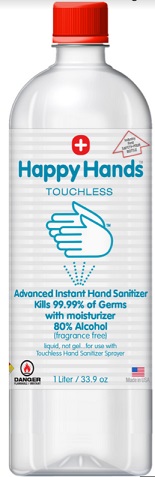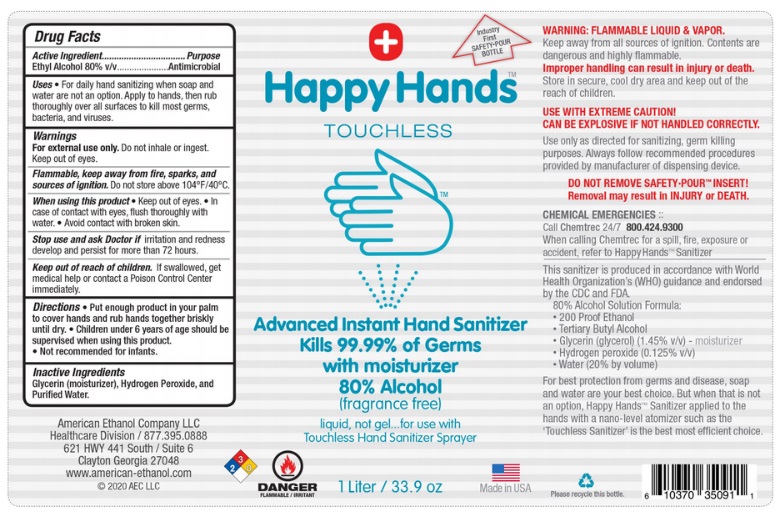 DRUG LABEL: HAPPY HANDS
NDC: 80849-001 | Form: LIQUID
Manufacturer: American Ethanol Company, LLC
Category: otc | Type: HUMAN OTC DRUG LABEL
Date: 20201026

ACTIVE INGREDIENTS: ALCOHOL 80 mL/100 mL
INACTIVE INGREDIENTS: GLYCERIN; HYDROGEN PEROXIDE; WATER

Active Ingredient

Ethyl Alcohol 80% v/v.

Purpose

Antimicrobial

Use

For daily hand sanitizing when soap and water are not an option. Apply to hands, then rub thoroughly over all surfaces to kill most germs, bacteria, and viruses.

Warnings

For external use only. Do not inhale or ingest. Keep out of eyes.

Flammable, keep away from fire, sparks, and sources of ignition. Do not store above 104°F/40°C.

When using this product Keep out of eyes. In case of contact with eyes, flush thoroughly with water. Avoid contact with broken skin.

Stop use and ask Doctor if irritation and redness develop and persist for more than 72 hours.

Keep out of reach of children. If swallowed, get medical help or contact a Poison Control Center right away.

Directions

- Put enough product in your palm to cover hands and rub hands together briskly until dry.
- Children under 6 years of age should be supervised when using this product.
- Not recommended for infants.

Inactive ingredients

Glycerin (moisturizer), Hydrogen Peroxide, and Purified Water.